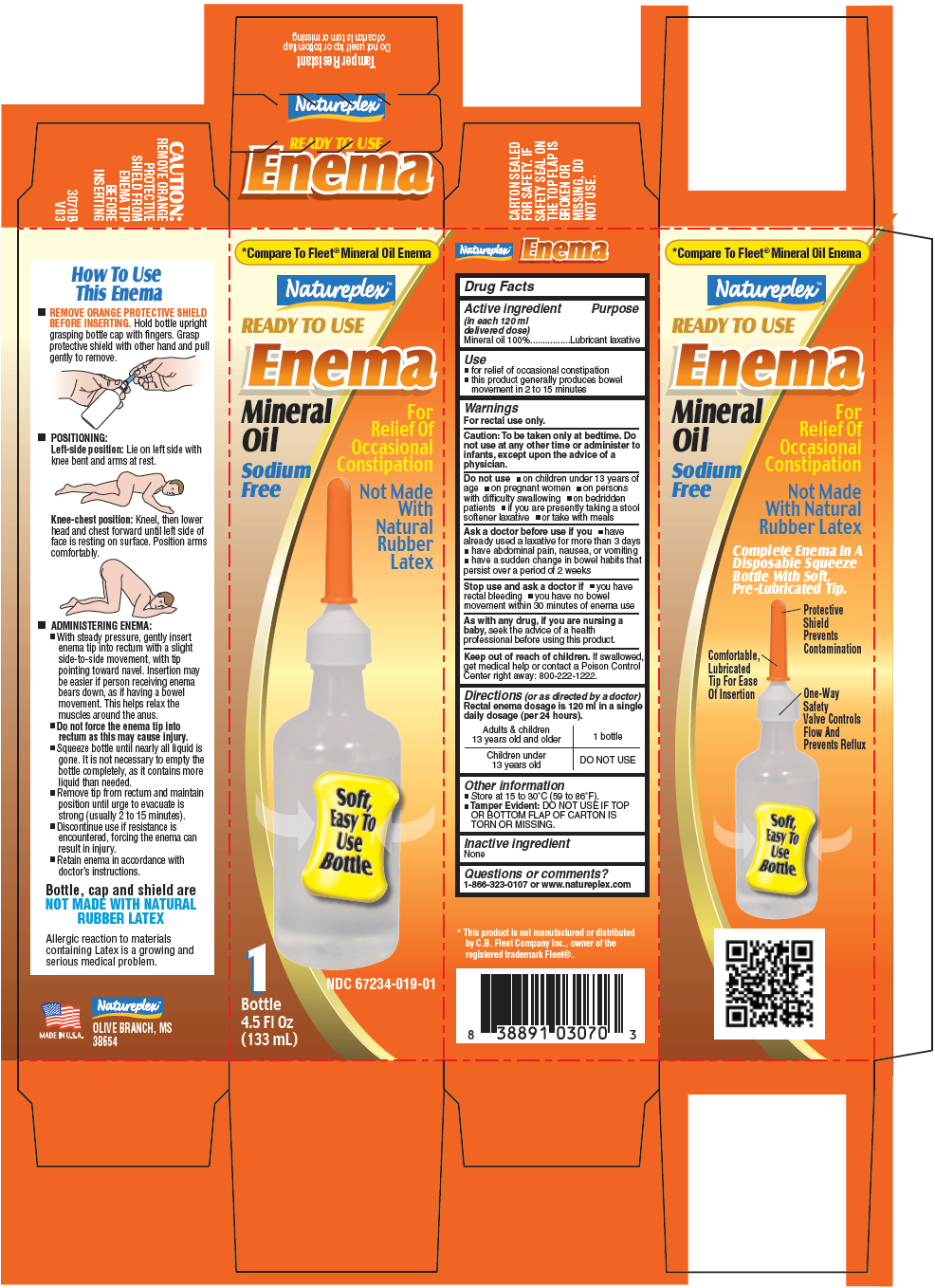 DRUG LABEL: Enema Mineral Oil
NDC: 67234-019 | Form: ENEMA
Manufacturer: Natureplex LLC
Category: otc | Type: HUMAN OTC DRUG LABEL
Date: 20241231

ACTIVE INGREDIENTS: Mineral Oil 118 g/118 mL

Enema Mineral Oil

Drug Facts

Active ingredient (in each 120 ml delivered dose)

Mineral oil 100%

Purpose

Lubricant laxative

Use

- for relief of occasional constipation
- this product generally produces bowel movement in 2 to 15 minutes

Warnings

For rectal use only.

Caution

To be taken only at bedtime. Do not use at any other time or administer to infants, except upon the advice of a physician.

Do not use

- on children under 13 years of age
- on pregnant women
- on persons with difficulty swallowing
- on bedridden patients
- if you are presently taking a stool softener laxative
- or take with meals

Ask a doctor before use if you

- have already used a laxative for more than 3 days
- have abdominal pain, nausea, or vomiting
- have a sudden change in bowel habits that persist over a period of 2 weeks

Stop use and ask a doctor if

- you have rectal bleeding
- you have no bowel movement within 30 minutes of enema use

PREGNANCY OR BREAST FEEDING

As with any drug, if you are nursing a baby, seek the advice of a health professional before using this product.

Keep out of reach of children. If swallowed, get medical help or contact a Poison Control Center right away: 800-222-1222.

Directions (or as directed by a doctor)

Rectal enema dosage is 120 ml in a single daily dosage (per 24 hours).

Adults & children 13 years old and older | 1 bottle
Children under 13 years old | DO NOT USE

Other information

- Store at 15 to 30°C (59 to 86°F).
- Tamper Evident: DO NOT USE IF TOP OR BOTTOM FLAP OF CARTON IS TORN OR MISSING.

Inactive ingredient

None

Questions or comments?

1-866-323-0107 or www.natureplex.com

PRINCIPAL DISPLAY PANEL - 133 mL Bottle Carton

*Compare To Fleet® Mineral Oil Enema

Natureplex™

READY TO USE

Enema

Mineral
Oil

Sodium
Free

For
Relief Of
Occasional
Constipation

Not Made
With
Natural
Rubber
Latex

Soft,
Easy To
Use
Bottle

NDC 67234-019-01

1
Bottle
4.5 Fl Oz
(133 mL)